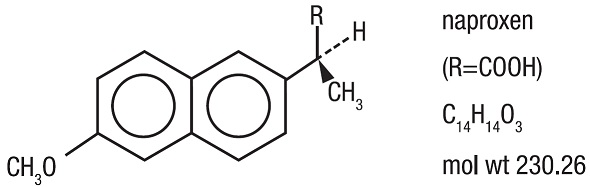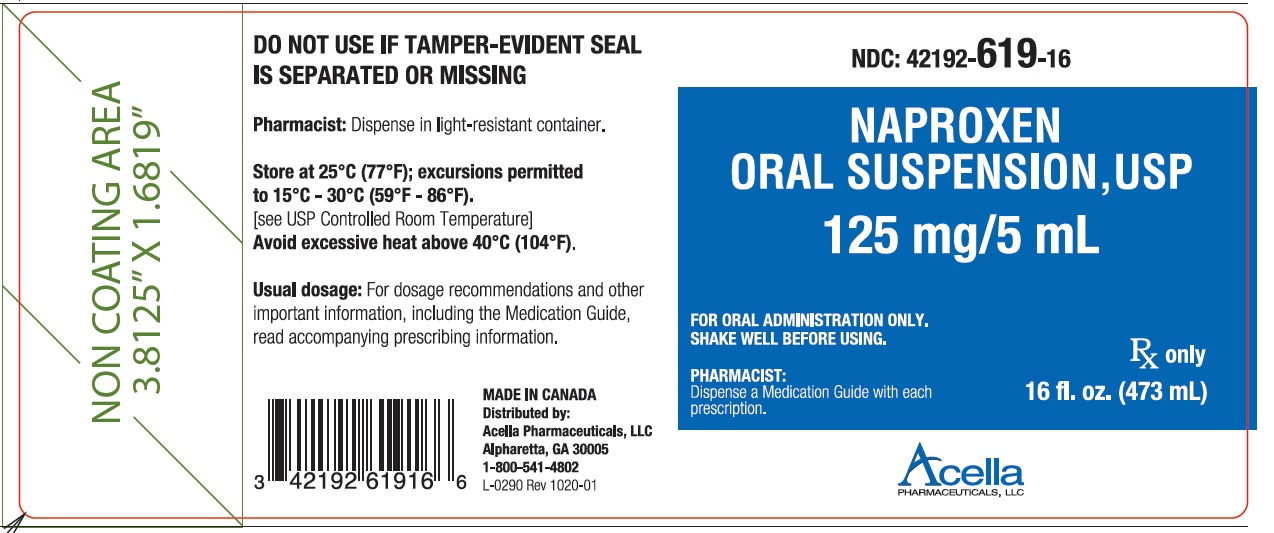 DRUG LABEL: Naproxen
NDC: 42192-619 | Form: SUSPENSION
Manufacturer: Acella Pharmaceuticals, LLC
Category: prescription | Type: HUMAN PRESCRIPTION DRUG LABEL
Date: 20260105

ACTIVE INGREDIENTS: NAPROXEN 125 mg/5 mL
INACTIVE INGREDIENTS: SUCROSE; MAGNESIUM ALUMINUM SILICATE; SORBITOL; SODIUM CHLORIDE; METHYLPARABEN; FUMARIC ACID; FD&C YELLOW NO. 6; PINEAPPLE; ORANGE; WATER

HIGHLIGHTS OF PRESCRIBING INFORMATION

These highlights do not include all the information needed to use NAPROXEN SUSPENSION safely and effectively. See full prescribing information for NAPROXEN SUSPENSION.
NAPROXEN suspension, for oral use
Initial U.S. Approval: 1976

WARNING: RISK OF SERIOUS CARDIOVASCULAR AND GASTROINTESTINAL EVENTS

See full prescribing information for complete boxed warning.

- Nonsteroidal anti-inflammatory drugs (NSAIDs) cause an increased risk of serious cardiovascular thrombotic events, including myocardial infarction and stroke, which can be fatal. This risk may occur early in treatment and may increase with duration of use. (5.1)
- Naproxen Suspension is contraindicated in the setting of coronary artery bypass graft (CABG) surgery. (4, 5.1)
- NSAIDs cause an increased risk of serious gastrointestinal (GI) adverse events including bleeding, ulceration, and perforation of the stomach or intestines, which can be fatal. These events can occur at any time during use and without warning symptoms. Elderly patients and patients with a prior history of peptic ulcer disease and/or GI bleeding are at greater risk for serious GI events. (5.2)

1 INDICATIONS AND USAGE

Naproxen Suspension is a non-steroidal anti-inflammatory drug indicated for:

the relief of the signs and symptoms of:

- rheumatoid arthritis
- osteoarthritis
- ankylosing spondylitis
- polyarticular juvenile idiopathic arthritis
- tendonitis
- bursitis
- acute gout

the management of:

- pain
- primary dysmenorrhea

2 DOSAGE AND ADMINISTRATION

Use the lowest effective dose for shortest duration consistent with individual patient treatment goals. (2)

Rheumatoid Arthritis, Osteoarthritis, and Ankylosing Spondylitis

Naproxen Suspension | 250 mg (10 mL) or 375 mg (15 mL) or 500 mg (20 mL) | twice daily twice daily twice daily

The dose may be adjusted up or down depending on the clinical response of the patient. In patients who tolerate lower doses well, the dose may be increased to naproxen 1500 mg/day for up to 6 months.

Polyarticular Juvenile Idiopathic Arthritis

Recommended total daily dose of naproxen is approximately 10 mg/kg given in 2 divided doses.

The following table may be used as a guide for dosing of naproxen suspension:

Patient’s Weight | Dose | Administered as
13 kg (29 lb) | 62.5 mg twice daily | 2.5 mL (1/2 tsp) twice daily
25 kg (55 lb) | 125 mg twice daily | 5.0 mL (1 tsp) twice daily
38 kg (84 lb) | 187.5 mg twice daily | 7.5 mL (1 1/2 tsp) twice daily

Management of Pain, Primary Dysmenorrhea, and Acute Tendonitis and Bursitis

The recommended starting dose of Naproxen Suspension is 500 mg (20 mL), followed by 250 mg (10 mL) every 6 to 8 hours as required.

Acute Gout

The recommended starting dose is 750 mg (30 mL) of Naproxen Suspension followed by 250 mg (10 mL) every 8 hours until the attack has subsided.

3 DOSAGE FORMS AND STRENGTHS

Naproxen Suspension: 125 mg/5 mL (contains 39 mg sodium)

4 CONTRAINDICATIONS

- Known hypersensitivity to naproxen or any components of the drug product (4)
- History of asthma, urticaria, or other allergic-type reactions after taking aspirin or other NSAIDs (4)
- In the setting of CABG surgery (4)

5 WARNINGS AND PRECAUTIONS

Hepatotoxicity:Inform patients of warning signs and symptoms of hepatotoxicity. Discontinue if abnormal liver tests persist or worsen or if clinical signs and symptoms of liver disease develop. (5.3Hepatotoxicity)

Hypertension:Patients taking some antihypertensive medications may have impaired response to these therapies when taking NSAIDs. Monitor blood pressure. (5.4, 7)

Heart Failure and Edema:Avoid use of Naproxen Suspension in patients with severe heart failure unless benefits are expected to outweigh risk of worsening heart failure. (5.5)

Renal Toxicity:Monitor renal function in patients with renal or hepatic impairment, heart failure, dehydration, or hypovolemia. Avoid use of Naproxen Suspension in patients with advanced renal disease unless benefits are expected to outweigh risk of worsening renal function. (5.6Renal Toxicity and Hyperkalemia)

Anaphylactic Reactions:Seek emergency help if an anaphylactic reaction occurs. (5.7)

Exacerbation of Asthma Related to Aspirin Sensitivity:Naproxen Suspension is contraindicated in patients with aspirin-sensitive asthma. Monitor patients with preexisting asthma (without aspirin sensitivity). (5.8)

Serious Skin Reactions:Discontinue Naproxen Suspension at first appearance of skin rash or other signs of hypersensitivity. (5.9)

Premature Closure of Fetal Ductus Arteriosus:Avoid use in pregnant women starting at 30 weeks gestation. (5.10, 8.1)

Hematologic Toxicity:Monitor hemoglobin or hematocrit in patients with any signs or symptoms of anemia. (5.11, 7)

6 ADVERSE REACTIONS

Most common adverse reactions to naproxen were dyspepsia, abdominal pain, nausea, headache, rash, ecchymosis, and edema. (6.1)

To report SUSPECTED ADVERSE REACTIONS, contact Pharmaceutical Associates, Inc. at 1-800-845-8210 or FDA at 1-800-FDA-1088 orwww.fda.gov/medwatch.

7 DRUG INTERACTIONS

Drugs that Interfere with Hemostasis (e.g. warfarin, aspirin, SSRIs/SNRIs):
Monitor patients for bleeding who are concomitantly taking Naproxen Suspension with drugs that interfere with hemostasis. Concomitant use of Naproxen Suspension and analgesic doses of aspirin is not generally recommended. (7)

ACE inhibitors, Angiotensin Receptor Blockers (ARB), or Beta-Blockers:Concomitant use with Naproxen Suspension may diminish the antihypertensive effect of these drugs. Monitor blood pressure. (7)

ACE Inhibitors and ARBs:Concomitant use with Naproxen Suspension in elderly, volume depleted, or those with renal impairment may result in deterioration of renal function. In such high risk patients, monitor for signs of worsening renal function. (7)

Diuretics:NSAIDs can reduce natriuretic effect of furosemide and thiazide diuretics. Monitor patients to assure diuretic efficacy including antihypertensive effects. (7)

Digoxin:Concomitant use with Naproxen Suspension can increase serum concentration and prolong half-life of digoxin. Monitor serum digoxin levels. (7)

8 USE IN SPECIFIC POPULATIONS

Pregnancy:Use of NSAIDs during the third trimester of pregnancy increases the risk of premature closure of the fetal ductus arteriosus. Avoid use of NSAIDs in pregnant women starting at 30 weeks gestation. (5.10, 8.1)

Infertility:NSAIDs are associated with reversible infertility. Consider withdrawal of Naproxen Suspension in women who have difficulties conceiving.(8.3)

Renal Impairment:Naproxen-containing products are not recommended for use in patients with moderate to severe and severe renal impairment (creatinine clearance <30 mL/min). (8.7)

FULL PRESCRIBING INFORMATION

WARNING: RISK OF SERIOUS CARDIOVASCULAR AND GASTROINTESTINAL EVENTS

Cardiovascular Thrombotic Events

- Nonsteroidal anti-inflammatory drugs (NSAIDs) cause an increased risk of serious cardiovascular thrombotic events, including myocardial infarction and stroke, which can be fatal. This risk may occur early in treatment and may increase with duration of use [ see Warnings and Precautions (5.1Cardiovascular Thrombotic Events)].
- Naproxen Suspension is contraindicated in the setting of coronary artery bypass graft (CABG) surgery [ see Contraindications (4), Warnings and Precautions (5.1Cardiovascular Thrombotic Events)].

Gastrointestinal Bleeding, Ulceration, and Perforation

- NSAIDs cause an increased risk of serious gastrointestinal (GI) adverse events including bleeding, ulceration, and perforation of the stomach or intestines, which can be fatal. These events can occur at any time during use and without warning symptoms. Elderly patients and patients with a prior history of peptic ulcer disease and/or GI bleeding are at greater risk for serious GI events [ see Warnings and Precautions (5.2) ] .

1 INDICATIONS AND USAGE

Naproxen Suspension is indicated for:

the relief of the signs and symptoms of:

- rheumatoid arthritis
- osteoarthritis
- ankylosing spondylitis
- polyarticular juvenile idiopathic arthritis
- tendonitis
- bursitis
- acute gout

the management of:

- pain
- primary dysmenorrhea

2 DOSAGE AND ADMINISTRATION

2.1 General Dosing Instructions

Carefully consider the potential benefits and risks of Naproxen Suspension and other treatment options before deciding to use Naproxen Suspension. Use the lowest effective dose for the shortest duration consistent with individual patient treatment goals [ see Warnings and Precautions (5) ].

After observing the response to initial therapy with Naproxen Suspension, the dose and frequency should be adjusted to suit an individual patient’s needs.

Always use a calibrated measuring device when administering Naproxen Suspension to ensure the dose is measured and administered accurately. A household teaspoon or tablespoon is not an adequate measuring device, especially when one-half of a teaspoonful is to be measured. Given the variability of the household spoon measure, it is strongly recommended that caregivers obtain and use a calibrated measuring device. Health care providers should recommend an appropriate measuring device that can measure and deliver the prescribed dose accurately, and instruct caregivers to use extreme caution in measuring the dosage.

Naproxen-containing products such as Naproxen Suspension, and other naproxen products should not be used concomitantly since they all circulate in the plasma as the naproxen anion.

2.2 Rheumatoid Arthritis, Osteoarthritis and Ankylosing Spondylitis

The recommended dosage of Naproxen Suspension is shown in Table 1.

Table 1: Recommended dosages of Naproxen Suspension
Naproxen Suspension | 250 mg (10 mL) or 375 mg (15 mL) or 500 mg (20 mL) | twice daily twice daily twice daily

Naproxen Suspension should be shaken gently before use.

During long-term administration, the dose of naproxen may be adjusted up or down depending on the clinical response of the patient. A lower daily dose may suffice for long-term administration. The morning and evening doses do not have to be equal in size and the administration of the drug more frequently than twice daily is not necessary.

The morning and evening doses do not have to be equal in size and administration of the drug more frequently than twice daily does not generally make a difference in response.

In patients who tolerate lower doses well, the dose may be increased to naproxen 1500 mg/day for limited periods of up to 6 months when a higher level of anti-inflammatory/analgesic activity is required. When treating such patients with naproxen 1500 mg/day, the physician should observe sufficient increased clinical benefits to offset the potential increased risk.

2.3 Polyarticular Juvenile Idiopathic Arthritis

The use of Naproxen Suspension is recommended for juvenile arthritis in children 2 years or older because it allows for more flexible dose titration based on the child’s weight. In pediatric patients, doses of 5 mg/kg/day produced plasma levels of naproxen similar to those seen in adults taking 500 mg of naproxen [ see Clinical Pharmacology (12 .3) ]

The recommended total daily dose of naproxen is approximately 10 mg/kg given in 2 divided doses (i.e., 5 mg/kg given twice a day). A measuring cup marked in 1/2 teaspoon and 2.5 milliliter increments is provided with the Naproxen Suspension. The following table may be used as a guide for dosing of Naproxen Suspension:

Patient’s Weight | Dose | Administered as
13 kg (29 lb) | 62.5 mg twice daily | 2.5 mL (1/2 tsp) twice daily
25 kg (55 lb) | 125 mg twice daily | 5.0 mL (1 tsp) twice daily
38 kg (84 lb) | 187.5 mg twice daily | 7.5 mL (1 1/2 tsp) twice daily

2.4 Management of Pain, Primary Dysmenorrhea, and Acute Tendonitis and Bursitis

The recommended starting dose of Naproxen Suspension is 500 mg (20 mL), followed by 250 mg (10 mL) every 6 to 8 hours as required. The total daily dose should not exceed 1250 mg (50 mL).

2.5 Acute Gout

The recommended starting dose is 750 mg (30 mL) of Naproxen Suspension followed by 250 mg (10 mL) every 8 hours until the attack has subsided.

2.6 Non-Interchangeability with Other Formulations of Naproxen

Different dose strengths and formulations (e.g., tablets, suspension) of naproxen are not interchangeable. This difference should be taken into consideration when changing strengths or formulations.

3 DOSAGE FORMS AND STRENGTHS

Naproxen Suspension: 125 mg/5 mL (contains 39 mg sodium): Available in 1 pint (473 mL) light-resistant bottles

4 CONTRAINDICATIONS

Naproxen Suspension is contraindicated in the following patients:

- Known hypersensitivity (e.g., anaphylactic reactions and serious skin reactions) to naproxen or any components of the drug product [ see Warnings and Precautions (5.7, 5.9) ]
- History of asthma, urticaria, or other allergic-type reactions after taking aspirin or other NSAIDs. Severe, sometimes fatal, anaphylactic reactions to NSAIDs have been reported in such patients [ see Warnings and Precautions (5.7, 5.8) ]
- In the setting of coronary artery bypass graft (CABG) surgery [ see Warnings and Precautions (5.1) ]

5 WARNINGS AND PRECAUTIONS

5.1 Cardiovascular Thrombotic Events

Clinical trials of several COX-2 selective and nonselective NSAIDs of up to three years duration have shown an increased risk of serious cardiovascular (CV) thrombotic events, including myocardial infarction (MI) and stroke, which can be fatal. Based on available data, it is unclear that the risk for CV thrombotic events is similar for all NSAIDs. The relative increase in serious CV thrombotic events over baseline conferred by NSAID use appears to be similar in those with and without known CV disease or risk factors for CV disease. However, patients with known CV disease or risk factors had a higher absolute incidence of excess serious CV thrombotic events, due to their increased baseline rate. Some observational studies found that this increased risk of serious CV thrombotic events began as early as the first weeks of treatment. The increase in CV thrombotic risk has been observed most consistently at higher doses.

To minimize the potential risk for an adverse CV event in NSAID-treated patients, use the lowest effective dose for the shortest duration possible. Physicians and patients should remain alert for the development of such events, throughout the entire treatment course, even in the absence of previous CV symptoms. Patients should be informed about the symptoms of serious CV events and the steps to take if they occur.

There is no consistent evidence that concurrent use of aspirin mitigates the increased risk of serious CV thrombotic events associated with NSAID use. The concurrent use of aspirin and an NSAID, such as naproxen, increases the risk of serious gastrointestinal (GI) events [ see Warnings and Precautions (5.2) ]

Status Post Coronary Artery Bypass Graft (CABG) Surgery
Two large, controlled clinical trials of a COX-2 selective NSAID for the treatment of pain in the first 10–14 days following CABG surgery found an increased incidence of myocardial infarction and stroke. NSAIDs are contraindicated in the setting of CABG [ see Contraindications (4) ]

Post-MI Patients
Observational studies conducted in the Danish National Registry have demonstrated that patients treated with NSAIDs in the post-MI period were at increased risk of reinfarction, CV-related death, and all-cause mortality beginning in the first week of treatment. In this same cohort, the incidence of death in the first year post-MI was 20 per 100 person years in NSAID-treated patients compared to 12 per 100 person years in non-NSAID exposed patients. Although the absolute rate of death declined somewhat after the first year post-MI, the increased relative risk of death in NSAID users persisted over at least the next four years of follow-up.

Avoid the use of Naproxen Suspension in patients with a recent MI unless the benefits are expected to outweigh the risk of recurrent CV thrombotic events. If Naproxen Suspension is used in patients with a recent MI, monitor patients for signs of cardiac ischemia.

5.2 Gastrointestinal Bleeding, Ulceration, and Perforation

NSAIDs, including naproxen, cause serious gastrointestinal (GI) adverse events including inflammation, bleeding, ulceration, and perforation of the esophagus, stomach, small intestine, or large intestine, which can be fatal. These serious adverse events can occur at any time, with or without warning symptoms, in patients treated with NSAIDS.

Only one in five patients who develop a serious upper GI adverse event on NSAID therapy is symptomatic. Upper GI ulcers, gross bleeding, or perforation caused by NSAIDs occurred in approximately 1% of patients treated for 3-6 months, and in about 2%-4% of patients treated for one year. However, even short-term NSAID therapy is not without risk.

Risk Factors for GI Bleeding, Ulceration, and Perforation
Patients with a prior history of peptic ulcer disease and/or GI bleeding who used NSAIDs had a greater than 10-fold increased risk for developing a GI bleed compared to patients without these risk factors. Other factors that increase the risk of GI bleeding in patients treated with NSAIDs include longer duration of NSAID therapy; concomitant use of oral corticosteroids, aspirin, anticoagulants, or selective serotonin reuptake inhibitors (SSRIs); smoking; use of alcohol; older age; and poor general health status. Most postmarketing reports of fatal GI events occurred in elderly or debilitated patients. Additionally, patients with advanced liver disease and/or coagulopathy are at increased risk for GI bleeding.

Strategies to Minimize the GI Risks in NSAID-treated patients:

- Use the lowest effective dosage for the shortest possible duration.
- Avoid administration of more than one NSAID at a time.
- Avoid use in patients at higher risk unless benefits are expected to outweigh the increased risk of bleeding. For such patients, as well as those with active GI bleeding, consider alternate therapies other than NSAIDs.
- Remain alert for signs and symptoms of GI ulceration and bleeding during NSAID therapy.
- If a serious GI adverse event is suspected, promptly initiate evaluation and treatment, and discontinue Naproxen Suspension until a serious GI adverse event is ruled out.
- In the setting of concomitant use of low-dose aspirin for cardiac prophylaxis, monitor patients more closely for evidence of GI bleeding [ see Drug Interactions (7) ]

5.3 Hepatotoxicity

Elevations of ALT or AST (three or more times the upper limit of normal [ULN]) have been reported in approximately 1% of NSAID-treated patients in clinical trials. In addition, rare, sometimes fatal, cases of severe hepatic injury, including fulminant hepatitis, liver necrosis, and hepatic failure have been reported.

Elevations of ALT or AST (less than three times ULN) may occur in up to 15% of patients treated with NSAIDs including naproxen.

Inform patients of the warning signs and symptoms of hepatotoxicity (e.g., nausea, fatigue, lethargy, diarrhea, pruritus, jaundice, right upper quadrant tenderness, and "flulike" symptoms). If clinical signs and symptoms consistent with liver disease develop, or if systemic manifestations occur (e.g., eosinophilia, rash, etc.), discontinue Naproxen Suspension immediately, and perform a clinical evaluation of the patient.

5.4 Hypertension

NSAIDs, including Naproxen Suspension, can lead to new onset of hypertension or worsening of pre-existing hypertension, either of which may contribute to the increased incidence of CV events. Patients taking angiotensin converting enzyme (ACE) inhibitors, thiazide diuretics, or loop diuretics may have impaired response to these therapies when taking NSAIDs [ see Drug Interactions (7) ].

Monitor blood pressure (BP) during the initiation of NSAID treatment and throughout the course of therapy.

5.5 Heart Failure and Edema

The Coxib and traditional NSAID Trialists’ Collaboration meta-analysis of randomized controlled trials demonstrated an approximately two-fold increase in hospitalizations for heart failure in COX-2 selective-treated patients and nonselective NSAID-treated patients compared to placebo-treated patients. In a Danish National Registry study of patients with heart failure, NSAID use increased the risk of MI, hospitalization for heart failure, and death.

Additionally, fluid retention and edema have been observed in some patients treated with NSAIDs. Use of naproxen may blunt the CV effects of several therapeutic agents used to treat these medical conditions (e.g., diuretics, ACE inhibitors, or angiotensin receptor blockers [ARBs]) [ see Drug Interactions (7) ].

Avoid the use of Naproxen Suspension in patients with severe heart failure unless the benefits are expected to outweigh the risk of worsening heart failure. If Naproxen Suspension is used in patients with severe heart failure, monitor patients for signs of worsening heart failure.

Each 5 mL of Naproxen Suspension contains 39 mg of sodium. This should be considered in patients whose overall intake of sodium must be severely restricted.

5.6 Renal Toxicity and Hyperkalemia

Renal Toxicity

Long-term administration of NSAIDs has resulted in renal papillary necrosis and other renal injury. Renal toxicity has also been seen in patients in whom renal prostaglandins have a compensatory role in the maintenance of renal perfusion. In these patients, administration of an NSAID may cause a dose-dependent reduction in prostaglandin formation and, secondarily, in renal blood flow, which may precipitate overt renal decompensation. Patients at greatest risk of this reaction are those with impaired renal function, dehydration, hypovolemia, heart failure, liver dysfunction, those taking diuretics and ACE inhibitors or ARBs, and the elderly. Discontinuation of NSAID therapy was usually followed by recovery to the pretreatment state.

No information is available from controlled clinical studies regarding the use of Naproxen Suspension in patients with advanced renal disease. The renal effects of Naproxen Suspension may hasten the progression of renal dysfunction in patients with preexisting renal disease.

Correct volume status in dehydrated or hypovolemic patients prior to initiating Naproxen Suspension. Monitor renal function in patients with renal or hepatic impairment, heart failure, dehydration, or hypovolemia during use of Naproxen Suspension [ see Drug Interactions (7) ]. Avoid the use of Naproxen Suspension in patients with advanced renal disease unless the benefits are expected to outweigh the risk of worsening renal function. If Naproxen Suspension is used in patients with advanced renal disease, monitor patients for signs of worsening renal function.

Hyperkalemia
Increases in serum potassium concentration, including hyperkalemia, have been reported with use of NSAIDs, even in some patients without renal impairment. In patients with normal renal function, these effects have been attributed to a hyporeninemic-hypoaldosteronism state.

5.7 Anaphylactic Reactions

Naproxen has been associated with anaphylactic reactions in patients with and without known hypersensitivity to naproxen and in patients with aspirin-sensitive asthma [ see Contraindications (4) and Warnings and Precautions (5.8) ]

Seek emergency help if an anaphylactic reaction occurs.

5.8 Exacerbation of Asthma Related to Aspirin Sensitivity

A subpopulation of patients with asthma may have aspirin-sensitive asthma which may include chronic rhinosinusitis complicated by nasal polyps; severe, potentially fatal bronchospasm; and/or intolerance to aspirin and other NSAIDs. Because cross-reactivity between aspirin and other NSAIDs has been reported in such aspirin-sensitive patients, Naproxen Suspension is contraindicated in patients with this form of aspirin sensitivity [ see Contraindications (4) ].When Naproxen Suspension is used in patients with preexisting asthma (without known aspirin sensitivity), monitor patients for changes in the signs and symptoms of asthma.

5.9 Serious Skin Reactions

NSAIDs, including naproxen can cause serious skin adverse reactions such as exfoliative dermatitis, Stevens-Johnson Syndrome (SJS), and toxic epidermal necrolysis (TEN), which can be fatal. These serious events may occur without warning. Inform patients about the signs and symptoms of serious skin reactions, and to discontinue the use of Naproxen Suspension at the first appearance of skin rash or any other sign of hypersensitivity. Naproxen Suspension is contraindicated in patients with previous serious skin reactions to NSAIDs [ see Contraindications (4) ].

5.10 Premature Closure of Fetal Ductus Arteriosus

Naproxen may cause premature closure of the fetal ductus arteriosus. Avoid use of NSAIDs, including Naproxen Suspension, in pregnant women starting at 30 weeks of gestation (third trimester) [ see Use in Specific Populations (8.1) ].

5.11 Hematologic Toxicity

Anemia has occurred in NSAID-treated patients. This may be due to occult or gross blood loss, fluid retention, or an incompletely described effect on erythropoiesis. If a patient treated with Naproxen Suspension has any signs or symptoms of anemia, monitor hemoglobin or hematocrit.

NSAIDs, including Naproxen Suspension, may increase the risk of bleeding events. Concomitant use of warfarin and other anticoagulants, antiplatelet agents (e.g., aspirin), serotonin reuptake inhibitors (SSRIs), and serotonin norepinephrine reuptake inhibitors (SNRIs) may increase this risk. Monitor these patients for signs of bleeding [ see Drug Interactions (7) ].

5.12 Masking of Inflammation and Fever

The pharmacological activity of Naproxen Suspension in reducing inflammation, and possibly fever, may diminish the utility of diagnostic signs in detecting infections.

5.13 Long-Term Use and Laboratory Monitoring

Because serious GI bleeding, hepatotoxicity, and renal injury can occur without warning symptoms or signs, consider monitoring patients on long-term NSAID treatment with a CBC and a chemistry profile periodically [ see Warnings and Precautions (5.2, 5.3Hepatotoxicity, 5.6Renal Toxicity and Hyperkalemia)].

Patients with initial hemoglobin values of 10 g or less who are to receive long-term therapy should have hemoglobin values determined periodically.

Because of adverse eye findings in animal studies with drugs of this class, it is recommended that ophthalmic studies be carried out if any change or disturbance in vision occurs.

6 ADVERSE REACTIONS

The following adverse reactions are discussed in greater detail in other sections of the labeling:

- Cardiovascular Thrombotic Events [ see Warnings and Precautions (5.1Cardiovascular Thrombotic Events)]
- GI Bleeding, Ulceration, and Perforation [ see Warnings and Precautions (5.2) ]
- Hepatotoxicity [ see Warnings and Precautions (5.3Hepatotoxicity)]
- Hypertension [ see Warnings and Precautions (5.4Hypertension)]
- Heart Failure and Edema [ see Warnings and Precautions (5.5Heart Failure and Edema)]
- Renal Toxicity and Hyperkalemia [ see Warnings and Precautions (5.6Renal Toxicity and Hyperkalemia)]
- Anaphylactic Reactions [ see Warnings and Precautions (5.7) ]
- Serious Skin Reactions [ see Warnings and Precautions (5.9) ]
- Hematologic Toxicity [ see Warnings and Precautions (5.11) ]

6.1 Clinical Trials Experience

Because clinical trials are conducted under widely varying conditions, adverse reaction rates observed in the clinical trials of a drug cannot be directly compared to rates in the clinical trials of another drug and may not reflect the rates observed in practice.

Adverse reactions reported in controlled clinical trials in 960 patients treated for rheumatoid arthritis or osteoarthritis are listed below. In general, reactions in patients treated chronically were reported 2 to 10 times more frequently than they were in short-term studies in the 962 patients treated for mild to moderate pain or for dysmenorrhea. The most frequent complaints reported related to the gastrointestinal tract.

A clinical study found gastrointestinal reactions to be more frequent and more severe in rheumatoid arthritis patients taking daily doses of 1500 mg naproxen compared to those taking 750 mg naproxen.

In controlled clinical trials with about 80 pediatric patients and in well-monitored, open-label studies with about 400 pediatric patients with polyarticular juvenile idiopathic arthritis treated with naproxen, the incidence of rash and prolonged bleeding times were greater, the incidence of gastrointestinal and central nervous system reactions were about the same, and the incidence of other reactions were lower in pediatric patients than in adults.

In patients taking naproxen in clinical trials, the most frequently reported adverse experiences in approximately 1% to 10% of patients are:

Gastrointestinal (GI) Experiences, including:heartburn*, abdominal pain*, nausea*, constipation*, diarrhea, dyspepsia, stomatitis

Central Nervous System:headache*, dizziness*, drowsiness*, lightheadedness, vertigo

Dermatologic:pruritus (itching)*, skin eruptions*, ecchymoses*, sweating, purpura

Special Senses:tinnitus*, visual disturbances, hearing disturbances

Cardiovascular:edema*, palpitations

General:dyspnea*, thirst

*Incidence of reported reaction between 3% and 9%. Those reactions occurring in less than 3% of the patients are unmarked.

In patients taking NSAIDs, the following adverse experiences have also been reported in approximately 1% to 10% of patients.

Gastrointestinal (GI) Experiences, including:flatulence, gross bleeding/perforation, GI ulcers (gastric/duodenal), vomiting

General:abnormal renal function, anemia, elevated liver enzymes, increased bleeding time, rashes

6.2 Postmarketing Experience

The following adverse reactions have been identified during post approval use of naproxen. Because these reactions are reported voluntarily from a population of uncertain size, it is not always possible to reliably estimate their frequency or establish a causal relationship to drug exposure.

The following are additional adverse experiences reported in <1% of patients taking naproxen during clinical trials and through postmarketing reports. Those adverse reactions observed through postmarketing reports are italicized.

Body as a Whole: anaphylactoid reactions, angioneurotic edema, menstrual disorders, pyrexia (chills and fever)

Cardiovascular: congestive heart failure, vasculitis, hypertension, pulmonary edema

Gastrointestinal: inflammation, bleeding (sometimes fatal, particularly in the elderly), ulceration, perforation and obstruction of the upper or lower gastrointestinal tract. Esophagitis, stomatitis, hematemesis, pancreatitis, vomiting, colitis, exacerbation of inflammatory bowel disease (ulcerative colitis, Crohn’s disease).

Hepatobiliary: jaundice, abnormal liver function tests, hepatitis (some cases have been fatal)

Hemic and Lymphatic: eosinophilia, leucopenia, melena, thrombocytopenia, agranulocytosis, granulocytopenia, hemolytic anemia, aplastic anemia

Metabolic and Nutritional: hyperglycemia, hypoglycemia

Nervous System: inability to concentrate, depression, dream abnormalities, insomnia, malaise, myalgia, muscle weakness, aseptic meningitis, cognitive dysfunction, convulsions

Respiratory: eosinophilic pneumonitis, asthma

Dermatologic: alopecia, urticaria, skin rashes, toxic epidermal necrolysis, erythema multiforme, erythema nodosum, fixed drug eruption, lichen planus, pustular reaction, systemic lupus erythematoses, bullous reactions, including Stevens-Johnson syndrome, photosensitive dermatitis, photosensitivity reactions, including rare cases resembling porphyria cutanea tarda (pseudoporphyria) or epidermolysis bullosa. If skin fragility, blistering or other symptoms suggestive of pseudoporphyria occur, treatment should be discontinued and the patient monitored.

Special Senses: hearing impairment, corneal opacity, papillitis, retrobulbar optic neuritis, papilledema

Urogenital: glomerular nephritis, hematuria, hyperkalemia, interstitial nephritis, nephrotic syndrome, renal disease, renal failure, renal papillary necrosis, raised serum creatinine

Reproduction (female): infertility

In patients taking NSAIDs, the following adverse experiences have also been reported in <1% of patients.

Body as a Whole: fever, infection, sepsis, anaphylactic reactions, appetite changes, death

Cardiovascular: hypertension, tachycardia, syncope, arrhythmia, hypotension, myocardial infarction

Gastrointestinal: dry mouth, esophagitis, gastric/peptic ulcers, gastritis, glossitis, eructation

Hepatobiliary: hepatitis, liver failure

Hemic and Lymphatic: rectal bleeding, lymphadenopathy, pancytopenia

Metabolic and Nutritional: weight changes Nervous System: anxiety, asthenia, confusion, nervousness, paresthesia, somnolence, tremors, convulsions, coma, hallucinations

Respiratory: asthma, respiratory depression, pneumonia

Dermatologic: exfoliative dermatitis

Special Senses: blurred vision, conjunctivitis

Urogenital: cystitis, dysuria, oliguria/polyuria, proteinuria

7 DRUG INTERACTIONS

See Table 2 for clinically significant drug interactions with naproxen.

Table 2: Clinically Significant Drug Interactions with Naproxen.
Drugs That Interfere with Hemostasis
Clinical Impact: | - Naproxen and anticoagulants such as warfarin have a synergistic effect on bleeding. The concomitant use of naproxen and anticoagulants have an increased risk of serious bleeding compared to the use of either drug alone. - Serotonin release by platelets plays an important role in hemostasis. Case-control and cohort epidemiological studies showed that concomitant use of drugs that interfere with serotonin reuptake and an NSAID may potentiate the risk of bleeding more than an NSAID alone.
Intervention: | Monitor patients with concomitant use of Naproxen Suspension with anticoagulants (e.g., warfarin), antiplatelet agents (e.g., aspirin), selective serotonin reuptake inhibitors (SSRIs), and serotonin norepinephrine reuptake inhibitors (SNRIs) for signs of bleeding [ see Warnings and Precautions (5.11) ].
Aspirin
Clinical Impact: | A pharmacodynamic (PD) study has demonstrated an interaction in which lower dose naproxen (220mg/day or 220mg twice daily) interfered with the antiplatelet effect of low-dose immediate-releaseaspirin, with the interaction most marked during the washout period of naproxen [ see Clinical Pharmacology (12.2) ]. There is reason to expect that the interaction would be present with prescription doses of naproxen or with enteric-coatedlow-dose aspirin; however, the peak interference with aspirin function may be later than observed in the PD study due to the longer washout period. Controlled clinical studies showed that the concomitant use of NSAIDs and analgesic doses of aspirin does not produce any greater therapeutic effect than the use of NSAIDs alone. In a clinical study, the concomitant use of an NSAID and aspirin was associated with a significantly increased incidence of GI adverse reactions as compared to use of the NSAID alone [ see Warnings and Precautions (5.2) ].
Intervention: | Because there may be an increased risk of cardiovascular events following discontinuation of naproxen due to the interference with the antiplatelet effect of aspirin during the washout period, for patients taking low-dose aspirin for cardioprotection who require intermittent analgesics, consider use of an NSAID that does not interfere with the antiplatelet effect of aspirin, or non-NSAID analgesics where appropriate. Concomitant use of Naproxen Suspension and analgesic doses of aspirin is not generally recommended because of the increased risk of bleeding [ see Warnings and Precautions (5.11) ]. Naproxen suspension is not a substitute for low dose aspirin for cardiovascular protection.
ACE Inhibitors, Angiotensin Receptor Blockers, and Beta-Blockers
Clinical Impact: | - NSAIDs may diminish the antihypertensive effect of angiotensin converting enzyme (ACE) inhibitors, angiotensin receptor blockers (ARBs), or beta-blockers (including propranolol). - In patients who are elderly, volume-depleted (including those on diuretic therapy), or have renal impairment, co-administration of an NSAID with ACE inhibitors or ARBs may result in deterioration of renal function, including possible acute renal failure. These effects are usually reversible.
Intervention: | During concomitant use of Naproxen Suspension and ACE-inhibitors, ARBs, or beta-blockers, monitor blood pressure to ensure that the desired blood pressure is obtained.; - During concomitant use of Naproxen Suspension and ACE-inhibitors or ARBs in patients who are elderly, volume-depleted, or have impaired renal function, monitor for signs of worsening renal function [ see Warnings and Precautions (5.6Renal Toxicity and Hyperkalemia)]. - When these drugs are administered concomitantly, patients should be adequately hydrated. Assess renal function at the beginning of the concomitant treatment and periodically thereafter.
Diuretics
Clinical Impact: | Clinical studies, as well as post-marketing observations, showed that NSAIDs reduced the natriuretic effect of loop diuretics (e.g., furosemide) and thiazide diuretics in some patients. This effect has been attributed to the NSAID inhibition of renal prostaglandin synthesis.
Intervention: | During concomitant use of Naproxen Suspension with diuretics, observe patients for signs of worsening renal function, in addition to assuring diuretic efficacy including antihypertensive effects [ see Warnings and Precautions (5.6Renal Toxicity and Hyperkalemia)].
Digoxin
Clinical Impact: | The concomitant use of naproxen with digoxin has been reported to increase the serum concentration and prolong the half-life of digoxin
Intervention: | During concomitant use of Naproxen Suspension and digoxin, monitor serum digoxin levels.
Lithium
Clinical Impact: | NSAIDs have produced elevations in plasma lithium levels and reductions in renal lithium clearance. The mean minimum lithium concentration increased 15%, and the renal clearance decreased by approximately 20%. This effect has been attributed to NSAID inhibition of renal prostaglandin synthesis.
Intervention: | During concomitant use of Naproxen Suspension and lithium, monitor patients for signs of lithium toxicity.
Methotrexate
Clinical Impact: | Concomitant use of NSAIDs and methotrexate may increase the risk for methotrexate toxicity (e.g., neutropenia, thrombocytopenia, renal dysfunction).
Intervention: | During concomitant use of Naproxen Suspension and methotrexate, monitor patients for methotrexate toxicity.
Cyclosporine
Clinical Impact: | Concomitant use of Naproxen Suspension and cyclosporine may increase cyclosporine’s nephrotoxicity.
Intervention: | During concomitant use of Naproxen Suspension and cyclosporine, monitor patients for signs of worsening renal function.
NSAIDs and Salicylates
Clinical Impact: | Concomitant use of naproxen with other NSAIDs or salicylates (e.g., diflunisal, salsalate) increases the risk of GI toxicity, with little or no increase in efficacy [ see Warnings and Precautions (5.2) ].
Intervention: | The concomitant use of naproxen with other NSAIDs or salicylates is not recommended.
Pemetrexed
Clinical Impact: | Concomitant use of Naproxen Suspension and pemetrexed may increase the risk of pemetrexed-associated myelosuppression, renal, and GI toxicity (see the pemetrexed prescribing information).
Intervention: | During concomitant use of Naproxen Suspension and pemetrexed, in patients with renal impairment whose creatinine clearance ranges from 45 to 79 mL/min, monitor for myelosuppression, renal and GI toxicity. NSAIDs with short elimination half-lives (e.g., diclofenac, indomethacin) should be avoided for a period of two days before, the day of, and two days following administration of pemetrexed. In the absence of data regarding potential interaction between pemetrexed and NSAIDs with longer half-lives (e.g., meloxicam, nabumetone), patients taking these NSAIDs should interrupt dosing for at least five days before, the day of, and two days following pemetrexed administration.
Antacids and Sucralfate
Clinical Impact: | Concomitant administration of some antacids (magnesium oxide or aluminum hydroxide) and sucralfate can delay the absorption of naproxen.
Intervention: | Concomitant administration of antacids such as magnesium oxide or aluminum hydroxide, and sucralfate with Naproxen Suspension is not recommended.
Cholestyramine
Clinical Impact: | Concomitant administration of cholestyramine can delay the absorption of naproxen.
Intervention: | Concomitant administration of cholestyramine with Naproxen Suspension is not recommended.
Probenecid
Clinical Impact: | Probenecid given concurrently increases naproxen anion plasma levels and extends its plasma half-life significantly.
Intervention: | Patients simultaneously receiving Naproxen Suspension and probenecid should be observed for adjustment of dose if required.
Other albumin-bound drugs
Clinical Impact: | Naproxen is highly bound to plasma albumin; it thus has a theoretical potential for interaction with other albumin-bound drugs such as coumarin-type anticoagulants, sulphonylureas, hydantoins, other NSAIDs, and aspirin [ see Warnings and Precautions (5.2) ]
Intervention: | Patients simultaneously receiving Naproxen Suspension and a hydantoin, sulphonamide or sulphonylurea should be observed for adjustment of dose if required.

Drug/Laboratory Test Interactions

Bleeding times
Clinical Impact: | Naproxen may decrease platelet aggregation and prolong bleeding time.
Intervention: | This effect should be kept in mind when bleeding times are determined.
Porter-Silber test
Clinical Impact: | The administration of naproxen may result in increased urinary values for 17-ketogenic steroids because of an interaction between the drug and/or its metabolites with m-di-nitrobenzene used in this assay.
Intervention: | Although 17-hydroxy-corticosteroid measurements (Porter-Silber test) do not appear to be artifactually altered, it is suggested that therapy with naproxen be temporarily discontinued 72 hours before adrenal function tests are performed if the Porter-Silber test is to be used.
Urinary assays of 5-hydroxy indoleacetic acid (5HIAA)
Clinical Impact: | Naproxen may interfere with some urinary assays of 5-hydroxy indoleacetic acid (5HIAA).
Intervention: | This effect should be kept in mind when urinary 5-hydroxy indoleacetic acid is determined.

8 USE IN SPECIFIC POPULATIONS

8.1 Pregnancy

Risk Summary

Use of NSAIDs, including Naproxen Suspension, during the third trimester of pregnancy increases the risk of premature closure of the fetal ductus arteriosus. Avoid use of NSAIDs, including Naproxen Suspension, in pregnant women starting at 30 weeks of gestation (third trimester).

There are no adequate and well-controlled studies of Naproxen Suspension in pregnant women.

Data from observational studies regarding potential embryofetal risks of NSAID use in women in the first or second trimesters of pregnancy are inconclusive. In the general U.S. population, all clinically recognized pregnancies, regardless of drug exposure, have a background rate of 2-4% for major malformations, and 15-20% for pregnancy loss. In animal reproduction studies in rats, rabbits, and mice no evidence of teratogenicity or fetal harm when naproxen was administered during the period of organogenesis at doses 0.13, 0.26, and 0.6 times the maximum recommended human daily dose of 1500 mg/day, respectively. Based on animal data, prostaglandins have been shown to have an important role in endometrial vascular permeability, blastocyst implantation, and decidualization. In animal studies, administration of prostaglandin synthesis inhibitors such as naproxen, resulted in increased pre- and post-implantation loss.

Clinical Considerations

Labor or Delivery

There are no studies on the effects of Naproxen Suspension during labor or delivery. In animal studies, NSAIDS, including naproxen, inhibit prostaglandin synthesis, cause delayed parturition, and increase the incidence of stillbirth.

Data

Human data

There is some evidence to suggest that when inhibitors of prostaglandin synthesis are used to delay preterm labor there is an increased risk of neonatal complications such as necrotizing enterocolitis, patent ductus arteriosus and intracranial hemorrhage. Naproxen treatment given in late pregnancy to delay parturition has been associated with persistent pulmonary hypertension, renal dysfunction and abnormal prostaglandin E levels in preterm infants. Because of the known effects of nonsteroidal anti-inflammatory drugs on the fetal cardiovascular system (closure of ductus arteriosus), use during pregnancy (particularly starting at 30 weeks of gestation, or third trimester) should be avoided.

Animal data

Reproduction studies have been performed in rats at 20 mg/kg/day (0.13 times the maximum recommended human daily dose of 1500 mg/day based on body surface area comparison), rabbits at 20 mg/kg/day (0.26 times the maximum recommended human daily dose, based on body surface area comparison), and mice at 170 mg/kg/day (0.6 times the maximum recommended human daily dose based on body surface area comparison) with no evidence of impaired fertility or harm to the fetus due to the drug. Based on animal data, prostaglandins have been shown to have an important role in endometrial vascular permeability, blastocyst implantation, and decidualization. In animal studies, administration of prostaglandin synthesis inhibitors such as naproxen, resulted in increased pre- and post-implantation loss.

8.2 Lactation

Risk Summary

The naproxen anion has been found in the milk of lactating women at a concentration equivalent to approximately 1% of maximum naproxen concentration in plasma. The developmental and health benefits of breastfeeding should be considered along with the mother’s clinical need for Naproxen Suspension and any potential adverse effects on the breastfed infant from the Naproxen Suspension or from the underlying maternal condition.

8.3 Females and Males of Reproductive Potential

Infertility

Females

Based on the mechanism of action, the use of prostaglandin-mediated NSAIDs, including Naproxen Suspension, may delay or prevent rupture of ovarian follicles, which has been associated with reversible infertility in some women. Published animal studies have shown that administration of prostaglandin synthesis inhibitors has the potential to disrupt prostaglandin-mediated follicular rupture required for ovulation. Small studies in women treated with NSAIDs have also shown a reversible delay in ovulation.

Consider withdrawal of NSAIDs, including Naproxen Suspension, in women who have difficulties conceiving or who are undergoing investigation of infertility.

8.4 Pediatric Use

Safety and effectiveness in pediatric patients below the age of 2 years have not been established. Pediatric dosing recommendations for polyarticular juvenile idiopathic arthritis are based on well-controlled studies. There are no adequate effectiveness or dose-response data for other pediatric conditions, but the experience in polyarticular juvenile idiopathic arthritis and other use experience have established that single doses of 2.5 to 5 mg/kg (as naproxen suspension), with total daily dose not exceeding 15 mg/kg/day, are well tolerated in pediatric patients over 2 years of age.

8.5 Geriatric Use

The hepatic and renal tolerability of long-term naproxen administration was studied in two double-blind clinical trials involving 586 patients. Of the patients studied, 98 patients were age 65 and older and 10 of the 98 patients were age 75 and older. Naproxen was administered at doses of 375 mg twice daily or 750 mg twice daily for up to 6 months. Transient abnormalities of laboratory tests assessing hepatic and renal function were noted in some patients, although there were no differences noted in the occurrence of abnormal values among different age groups.

Elderly patients, compared to younger patients, are at greater risk for NSAID-associated serious cardiovascular, gastrointestinal, and/or renal adverse reactions. If the anticipated benefit for the elderly patient outweighs these potential risks, start dosing at the low end of the dosing range, and monitor patients for adverse effects [ see Warnings and Precautions (5.1Cardiovascular Thrombotic Events, 5.2, 5.3Hepatotoxicity, 5.6Renal Toxicity and Hyperkalemia, 5.13) ].

Studies indicate that although total plasma concentration of naproxen is unchanged, the unbound plasma fraction of naproxen is increased in the elderly. The clinical significance of this finding is unclear, although it is possible that the increase in free naproxen concentration could be associated with an increase in the rate of adverse events per a given dosage in some elderly patients. Caution is advised when high doses are required and some adjustment of dosage may be required in elderly patients. As with other drugs used in the elderly, it is prudent to use the lowest effective dose.

Experience indicates that geriatric patients may be particularly sensitive to certain adverse effects of nonsteroidal anti-inflammatory drugs. Elderly or debilitated patients seem to tolerate peptic ulceration or bleeding less well when these events do occur. Most spontaneous reports of fatal GI events are in the geriatric population [ see Warnings and Precautions (5.6Renal Toxicity and Hyperkalemia)].

Naproxen is known to be substantially excreted by the kidney, and the risk of toxic reactions to this drug may be greater in patients with impaired renal function. Because elderly patients are more likely to have decreased renal function, care should be taken in dose selection, and it may be useful to monitor renal function. Geriatric patients may be at a greater risk for the development of a form of renal toxicity precipitated by reduced prostaglandin formation during administration of nonsteroidal anti-inflammatory drugs [ see Warnings and Precautions (5.6Renal Toxicity and Hyperkalemia)].

8.6 Hepatic Impairment

Caution is advised when high doses are required and some adjustment of dosage may be required in these patients. It is prudent to use the lowest effective dose [ see Clinical Pharmacology (12.3) ].

8.7 Renal Impairment

Naproxen-containing products are not recommended for use in patients with moderate to severe and severe renal impairment (creatinine clearance <30 mL/min) [ see Warnings and Precautions (5.6), Clinical Pharmacology (12.3) ].

10 OVERDOSAGE

Symptoms following acute NSAID overdosages have been typically limited to lethargy, drowsiness, nausea, vomiting, and epigastric pain, which have been generally reversible with supportive care. Gastrointestinal bleeding has occurred. Hypertension, acute renal failure, respiratory depression, and coma have occurred, but were rare. A few patients have experienced convulsions, but it is not clear whether or not these were drug-related. It is not known what dose of the drug would be life threatening [ see Warnings and Precautions (5.1Cardiovascular Thrombotic Events, 5.2].

Manage patients with symptomatic and supportive care following an NSAID overdosage. There are no specific antidotes. There are no specific antidotes. Hemodialysis does not decrease the plasma concentration of naproxen because of the high degree of its protein binding. Consider emesis and/or activated charcoal (60 to 100 grams in adults, 1 to 2 grams per kg of body weight in pediatric patients) and/or osmotic cathartic in symptomatic patients seen within four hours of ingestion or in patients with a large overdosage (5 to 10 times the recommended dosage). Forced diuresis, alkalinization of urine, hemodialysis, or hemoperfusion may not be useful due to high protein binding.

For additional information about overdosage treatment contact a poison control center (1-800-222-1222).

11 DESCRIPTION

Naproxen Suspension (naproxen) is available as a light orange-colored opaque oral suspension containing 125 mg/5 mL of naproxen for oral administration.

Naproxen is a propionic acid derivative related to the arylacetic acid group of nonsteroidal anti-inflammatory drugs. The chemical name is (S)-6-methoxy-α-methyl-2-naphthaleneacetic acid. The molecular weight is 230.26 Its molecular formula is C14H14O3, and it has the following chemical structure.

Naproxen is an odorless, white to off-white crystalline substance. It is lipid-soluble, practically insoluble in water at low pH and freely soluble in water at high pH. The octanol/water partition coefficient of naproxen at pH 7.4 is 1.6 to 1.8.

The inactive ingredients in Naproxen Suspension include sucrose, magnesium aluminum silicate, sorbitol solution and sodium chloride (39 mg/5 mL, 1.5 mEq), methylparaben, fumaric acid, FD&C Yellow No. 6, imitation pineapple flavor, imitation orange flavor and purified water. The pH of the suspension ranges from 2.2 to 3.7.

12 CLINICAL PHARMACOLOGY

12.1 Mechanism of Action

Naproxen has analgesic, anti-inflammatory, and antipyretic properties.

The mechanism of action of naproxen, like that of other NSAIDs, is not completely understood but involves inhibition of cyclooxygenase (COX-1 and COX-2).

Naproxen is a potent inhibitor of prostaglandin synthesis in vitro. Naproxen concentrations reached during therapy have produced in vivo effects. Prostaglandins sensitize afferent nerves and potentiate the action of bradykinin in inducing pain in animal models. Prostaglandins are mediators of inflammation. Because naproxen is an inhibitor of prostaglandin synthesis, its mode of action may be due to a decrease of prostaglandins in peripheral tissues.

12.2 Pharmacodynamics

In a healthy volunteer study, 10 days of concomitant administration of naproxen 220 mg once-daily with low-dose immediate-release aspirin (81 mg) showed an interaction with the antiplatelet activity of aspirin as measured by % serum thromboxane B2 inhibition at 24 hours following the day 10 dose [98.7% (aspirin alone) vs 93.1% (naproxen and aspirin)]. The interaction was observed even following discontinuation of naproxen on day 11 (while aspirin dose was continued) but normalized by day 13. In the same study, the interaction was greater when naproxen was administered 30 minutes prior to aspirin [98.7% vs 87.7%] and minimal when aspirin was administered 30 minutes prior to naproxen [98.7% vs 95.4%].

Following administration of naproxen 220 mg twice-daily with low-dose immediate release aspirin (first naproxen dose given 30 minutes prior to aspirin), the interaction was minimal at 24 h following day 10 dose [98.7% vs 95.7%]. However, the interaction was more prominent after discontinuation of naproxen (washout) on day 11 [98.7% vs 84.3%] and did not normalize completely by day 13 [98.5% vs 90.7%]. [ see Drug Interactions (7) ].

12.3 Pharmacokinetics

Naproxen is rapidly and completely absorbed from the gastrointestinal tract with an in vivo bioavailability of 95%. The elimination half-life of naproxen ranges from 12 to 17 hours. Steady-state levels of naproxen are reached in 4 to 5 days, and the degree of naproxen accumulation is consistent with this half-life.

Absorption

Peak plasma levels of naproxen given as Naproxen Suspension are attained in 1 to 4 hours.
When Naproxen Suspension and immediate release naproxen tablets were given to fasted subjects (n=12) in a single-dose, crossover study, there were comparable pharmacokinetic parameters between the two formulations.

 | Naproxen Suspension | Naproxen Tablets 500 mg
Cmax(µg/mL) | 64.3 | 71.1
Tmax(hours) | 2.6 | 2.3
T1/2(hours) | 16.8 | 16.3
AUC0–t(µg·hr/mL) | 1249 | 1218

Distribution

Naproxen has a volume of distribution of 0.16 L/kg. At therapeutic levels naproxen is greater than 99% albumin-bound. At doses of naproxen greater than 500 mg/day there is less than proportional increase in plasma levels due to an increase in clearance caused by saturation of plasma protein binding at higher doses (average trough Css 36.5, 49.2 and 56.4 mg/L with 500, 1000 and 1500 mg daily doses of naproxen, respectively). The naproxen anion has been found in the milk of lactating women at a concentration equivalent to approximately 1% of maximum naproxen concentration in plasma (see PRECAUTIONS; Nursing Mothers).

Elimination

Metabolism

Naproxen is extensively metabolized in the liver to 6-0-desmethyl naproxen, and both parent and metabolites do not induce metabolizing enzymes. Both naproxen and 6-0-desmethyl naproxen are further metabolized to their respective acylglucuronide conjugated metabolites.

Excretion

The clearance of naproxen is 0.13 mL/min/kg. Approximately 95% of the naproxen from any dose is excreted in the urine, primarily as naproxen (<1%), 6-0-desmethyl naproxen (<1%) or their conjugates (66% to 92%). The plasma half-life of the naproxen anion in humans ranges from 12 to 17 hours. The corresponding half-lives of both naproxen’s metabolites and conjugates are shorter than 12 hours, and their rates of excretion have been found to coincide closely with the rate of naproxen clearance from the plasma. Small amounts, 3% or less of the administered dose, are excreted in the feces. In patients with renal failure metabolites may accumulate [ see Warnings and Precautions (5.6) ].

Specific Populations

Pediatric

In pediatric patients aged 5 to 16 years with arthritis, plasma naproxen levels following a 5 mg/kg single dose of naproxen suspension [ see Dosage and Administration (2) ] were found to be similar to those found in normal adults following a 500 mg dose. The terminal half-life appears to be similar in pediatric and adult patients. Pharmacokinetic studies of naproxen were not performed in pediatric patients younger than 5 years of age. Pharmacokinetic parameters appear to be similar following administration of Naproxen suspension or tablets in pediatric patients.

Geriatric

Studies indicate that although total plasma concentration of naproxen is unchanged, the unbound plasma fraction of naproxen is increased in the elderly, although the unbound fraction is <1% of the total naproxen concentration. Unbound trough naproxen concentrations in elderly subjects have been reported to range from 0.12% to 0.19% of total naproxen concentration, compared with 0.05% to 0.075% in younger subjects.

Hepatic Impairment

Naproxen pharmacokinetics has not been determined in subjects with hepatic insufficiency.

Chronic alcoholic liver disease and probably other diseases with decreased or abnormal plasma proteins (albumin) reduce the total plasma concentration of naproxen, but the plasma concentration of unbound naproxen is increased.

Renal Impairment

Naproxen pharmacokinetics has not been determined in subjects with renal insufficiency. Given that naproxen, its metabolites and conjugates are primarily excreted by the kidney, the potential exists for naproxen metabolites to accumulate in the presence of renal insufficiency. Elimination of naproxen is decreased in patients with severe renal impairment.

Drug Interaction Studies

Aspirin
When NSAIDs were administered with aspirin, the protein binding of NSAIDs were reduced, although the clearance of free NSAID was not altered. The clinical significance of this interaction is not known. See Table 2 for clinically significant drug interactions of NSAIDs with aspirin [ see Drug Interactions (7) ].

13 NONCLINICAL TOXICOLOGY

13.1 Carcinogenesis, Mutagenesis, Impairment of Fertility

Carcinogenesis

A 2-year study was performed in rats to evaluate the carcinogenic potential of naproxen at rat doses of 8, 16, and 24 mg/kg/day (0.05, 0.1, and 0.16 times the maximum recommended human daily dose of 1500 mg/day based on a body surface area comparison). No evidence of tumorigenicity was found.

Mutagenesis

Naproxen tested positive in the in vivo sister chromatid exchange assay for but was not mutagenic in the in vitro bacterial reverse mutation assay (Ames test).

Impairment of Fertility

Male rats were treated with 2, 5, 10, and 20 mg/kg naproxen by oral gavage for 60 days prior to mating and female rats were treated with the same doses for 14 days prior to mating and for the first 7 days of pregnancy. There were no adverse effects on fertility noted (up to 0.13 times the MRDH based on body surface area).

14 CLINICAL STUDIES

Naproxen has been studied in patients with rheumatoid arthritis, osteoarthritis, polyarticular juvenile idiopathic arthritis, ankylosing spondylitis, tendonitis and bursitis, and acute gout. Improvement in patients treated for rheumatoid arthritis was demonstrated by a reduction in joint swelling, a reduction in duration of morning stiffness, a reduction in disease activity as assessed by both the investigator and patient, and by increased mobility as demonstrated by a reduction in walking time. Generally, response to naproxen has not been found to be dependent on age, sex, severity or duration of rheumatoid arthritis.

In patients with osteoarthritis, the therapeutic action of naproxen has been shown by a reduction in joint pain or tenderness, an increase in range of motion in knee joints, increased mobility as demonstrated by a reduction in walking time, and improvement in capacity to perform activities of daily living impaired by the disease.

In a clinical trial comparing standard formulations of naproxen 375 mg twice a day (750 mg a day) vs 750 mg twice a day (1500 mg/day), 9 patients in the 750 mg group terminated prematurely because of adverse events. Nineteen patients in the 1500 mg group terminated prematurely because of adverse events. Most of these adverse events were gastrointestinal events.

In clinical studies in patients with rheumatoid arthritis, osteoarthritis, and polyarticular juvenile idiopathic arthritis, naproxen has been shown to be comparable to aspirin and indomethacin in controlling the aforementioned measures of disease activity, but the frequency and severity of the milder gastrointestinal adverse effects (nausea, dyspepsia, heartburn) and nervous system adverse effects (tinnitus, dizziness, lightheadedness) were less in naproxen-treated patients than in those treated with aspirin or indomethacin.

In patients with ankylosing spondylitis, naproxen has been shown to decrease night pain, morning stiffness and pain at rest. In double-blind studies the drug was shown to be as effective as aspirin, but with fewer side effects.

In patients with acute gout, a favorable response to naproxen was shown by significant clearing of inflammatory changes (e.g., decrease in swelling, heat) within 24 to 48 hours, as well as by relief of pain and tenderness.

Naproxen has been studied in patients with mild to moderate pain secondary to postoperative, orthopedic, postpartum episiotomy and uterine contraction pain and dysmenorrhea. Onset of pain relief can begin within 1 hour in patients taking naproxen. Analgesic effect was shown by such measures as reduction of pain intensity scores, increase in pain relief scores, decrease in numbers of patients requiring additional analgesic medication, and delay in time to remedication. The analgesic effect has been found to last for up to 12 hours.

Naproxen may be used safely in combination with gold salts and/or corticosteroids; however, in controlled clinical trials, when added to the regimen of patients receiving corticosteroids, it did not appear to cause greater improvement over that seen with corticosteroids alone. Whether naproxen has a “steroid-sparing” effect has not been adequately studied. When added to the regimen of patients receiving gold salts, naproxen did result in greater improvement. Its use in combination with salicylates is not recommended because there is evidence that aspirin increases the rate of excretion of naproxen and data are inadequate to demonstrate that naproxen and aspirin produce greater improvement over that achieved with aspirin alone. In addition, as with other NSAIDs, the combination may result in higher frequency of adverse events than demonstrated for either product alone.

In^51Cr blood loss and gastroscopy studies with normal volunteers, daily administration of 1000 mg of Naproxen has been demonstrated to cause statistically significantly less gastric bleeding and erosion than 3250 mg of aspirin.

16 HOW SUPPLIED/STORAGE AND HANDLING

Naproxen Oral Suspension USP: 125 mg/5 mL (contains 39 mg sodium): Available in 1 pint (473 mL) light-resistant bottles

NDC - 42192-619-16

Storage
Store at 20° to 25°C (68° to 77°F). [See USP Controlled Room Temperature]

Avoid excessive heat above 40°C (104°F). Shake gently before use.

17 PATIENT COUNSELING INFORMATION

Advise the patient and caregiver to read the FDA-approved patient labeling (Medication Guide) that accompanies each prescription dispensed. Inform patients, families, or their caregivers should be informed of the following information before initiating therapy with Naproxen Suspension and periodically during the course of ongoing therapy.

Cardiovascular Thrombotic Events

Advise patients to be alert for the symptoms of cardiovascular thrombotic events, including chest pain, shortness of breath, weakness, or slurring of speech, and to report any of these symptoms to their health care provider immediately [ see Warnings and Precautions (5.1Cardiovascular Thrombotic Events)].

Gastrointestinal Bleeding, Ulceration, and Perforation

Advise patients to report symptoms of ulcerations and bleeding, including epigastric pain, dyspepsia, melena, and hematemesis to their health care provider. In the setting of concomitant use of low-dose aspirin for cardiac prophylaxis, inform patients of the increased risk for and the signs and symptoms of GI bleeding [ see Warnings and Precautions (5.2) ].

Hepatotoxicity

Inform patients of the warning signs and symptoms of hepatotoxicity (e.g., nausea, fatigue, lethargy, pruritus, diarrhea, jaundice, right upper quadrant tenderness, and “flu-like” symptoms). If these occur, instruct patients to stop Naproxen Suspension and seek immediate medical therapy [ see Warnings and Precautions (5.3Hepatotoxicity)].

Heart Failure and Edema

Advise patients to be alert for the symptoms of congestive heart failure including shortness of breath, unexplained weight gain, or edema and to contact their healthcare provider if such symptoms occur [ see Warnings and Precautions (5.5Heart Failure and Edema)].

Anaphylactic Reactions

Inform patients of the signs of an anaphylactic reaction (e.g., difficulty breathing, swelling of the face or throat). Instruct patients to seek immediate emergency help if these occur [ see Contraindications (4) and Warnings and Precautions (5.7) ].

Serious Skin Reactions

Advise patients to stop Naproxen Suspension immediately if they develop any type of rash and to contact their healthcare provider as soon as possible [ see Warnings and Precautions (5.9) ].

Female Fertility

Advise females of reproductive potential who desire pregnancy that NSAIDs, including Naproxen Suspension, may be associated with a reversible delay in ovulation [ see Use in Specific Populations (8.3) ].

Fetal Toxicity

Inform pregnant women to avoid use of Naproxen Suspension and other NSAIDs starting at 30 weeks gestation because of the risk of the premature closing of the fetal ductus arteriosus [ see Warnings and Precautions (5.10) and Use in Specific Populations (8.1) ].

Avoid Concomitant Use of NSAIDs

Inform patients that the concomitant use of Naproxen Suspension with other NSAIDs or salicylates (e.g., diflunisal, salsalate) is not recommended due to the increased risk of gastrointestinal toxicity, and little or no increase in efficacy [ see Warnings and Precautions (5.2) and Drug Interactions (7) ]. Alert patients that NSAIDs may be present in “over the counter” medications for treatment of colds, fever, or insomnia.

Use of NSAIDS and Low-Dose Aspirin

Inform patients not to use low-dose aspirin concomitantly with Naproxen Suspension until they talk to their healthcare provider [ see Drug Interactions (7) ].

Dosing Instructions

Instruct patients on how to measure and take the correct dose of Naproxen Suspension and to always use a calibrated measuring device when administering Naproxen Suspension to ensure the dose is measured and administered accurately [ see Dosage and Administration (2.1) ].

If the prescribed concentration is changed, instruct patients on how to correctly measure the new dose to avoid errors.

Made in Canada

Distributed by:

Acella Pharmaceutical, LLC

Alpharetta, GA 30005

L-0291 Rev 1020-01

For more information call 1-800-541-4802

Revised: October 2020

PATIENT INFORMATION

Medication Guide for Nonsteroidal Anti-inflammatory Drugs (NSAIDs)

What is the most important information I should know about medicines called Nonsteroidal Anti-inflammatory Drugs (NSAIDs)?
NSAIDs can cause serious side effects, including:

- Increased risk of a heart attack or stroke that can lead to death. This risk may happen early in treatment and may increase:
  - with increasing doses of NSAIDs
  - with longer use of NSAIDs
  Do not take NSAIDs right before or after a heart surgery called a “coronary artery bypass graft (CABG)."
  Avoid taking NSAIDs after a recent heart attack, unless your healthcare provider tells you to. You may have an increased risk of another heart attack if you take NSAIDs after a recent heart attack.

- Increased risk of bleeding, ulcers, and tears (perforation) of the esophagus (tube leading from the mouth to the stomach), stomach and intestines:
  - anytime during use
  - without warning symptoms
  - that may cause death
  The risk of getting an ulcer or bleeding increases with:
  - past history of stomach ulcers, or stomach or intestinal bleeding with use of NSAIDs
  - taking medicines called “corticosteroids”, “anticoagulants”, “SSRIs”, or “SNRIs”
  - increasing doses of NSAIDs
  - longer use of NSAIDs
  - smoking
  - drinking alcohol
  - older age
  - poor health
  - advanced liver disease
  - bleeding problems

NSAIDs should only be used:

- exactly as prescribed
- at the lowest dose possible for your treatment
- for the shortest time needed

What are NSAIDs?
NSAIDs are used to treat pain and redness, swelling, and heat (inflammation) from medical conditions such as different types of arthritis, menstrual cramps, and other types of short-term pain.

Who should not take NSAIDs?
Do not take NSAIDs:

- if you have had an asthma attack, hives, or other allergic reaction with aspirin or any other NSAIDs.
- right before or after heart bypass surgery.

How should I take Naproxen Suspension?

Use ONLY a calibrated measuring device to measure your dose of Naproxen Suspension. DO NOT use a household teaspoon or tablespoon. Your pharmacist can provide you with the proper device to correctly measure your dose.

Before taking NSAIDS, tell your healthcare provider about all of your medical conditions, including if you:

- have liver or kidney problems
- have high blood pressure
- have asthma
- are pregnant or plan to become pregnant. Talk to your healthcare provider if you are considering taking NSAIDs during pregnancy. You should not take NSAIDs after 29 weeks of pregnancy.
- are breastfeeding or plan to breast feed.

Tell your healthcare provider about all of the medicines you take, including prescription or over-the-counter medicines, vitamins or herbal supplements.NSAIDs and some other medicines can interact with each other and cause serious side effects. Do not start taking any new medicine without talking to your healthcare provider first.

What are the possible side effects of NSAIDs?
NSAIDs can cause serious side effects, including:
See “What is the most important information I should know about medicines called Nonsteroidal Anti-inflammatory Drugs (NSAIDs)?”

- new or worse high blood pressure
- heart failure
- liver problems including liver failure
- kidney problems including kidney failure
- low red blood cells (anemia)
- life-threatening skin reactions
- life-threatening allergic reactions
- Other side effects of NSAIDs include:stomach pain, constipation, diarrhea, gas, heartburn, nausea, vomiting, and dizziness.

Get emergency help right away if you get any of the following symptoms:

- shortness of breath or trouble breathing
- chest pain
- weakness in one part or side of your body

- slurred speech
- swelling of the face or throat

Stop taking your NSAID and call your healthcare provider right away if you get any of the following symptoms:

- nausea
- more tired or weaker than usual
- diarrhea
- itching
- your skin or eyes look yellow
- indigestion or stomach pain
- flu-like symptoms

- vomit blood
- there is blood in your bowel movement or it is black and sticky like tar
- unusual weight gain
- skin rash or blisters with fever
- swelling of the arms, legs, hands and feet

If you take too much of your NSAID, call your healthcare provider or get medical help right away.
These are not all the possible side effects of NSAIDs. For more information, ask your healthcare provider or pharmacist about NSAIDs.
Call your doctor for medical advice about side effects. You may report side effects to FDA at 1-800-FDA-1088.

Other information about NSAIDs

- Aspirin is an NSAID but it does not increase the chance of a heart attack. Aspirin can cause bleeding in the brain, stomach, and intestines. Aspirin can also cause ulcers in the stomach and intestines.
- Some NSAIDs are sold in lower doses without a prescription (over-the counter). Talk to your healthcare provider before using over-the-counter NSAIDs for more than 10 days.

General information about the safe and effective use of NSAIDs
Medicines are sometimes prescribed for purposes other than those listed in a Medication Guide. Do not use NSAIDs for a condition for which it was not prescribed. Do not give NSAIDs to other people, even if they have the same symptoms that you have. It may harm them.
If you would like more information about NSAIDs, talk with your healthcare provider. You can ask your pharmacist or healthcare provider for information about NSAIDs that is written for health professionals.

Manufactured for:

Acella Pharmaceuticals, LLC

Alpharetta, GA 30005

For more information call 1-800-541-4802

This Medication Guide has been approved by the U.S. Food and Drug Administration.

Issued or Revised: October 2020

PRINCIPAL DISPLAY PANEL

NDC 42192-619-16

Naproxen Oral Suspension USP

125 mg/5 mL (contains 39 mg sodium)